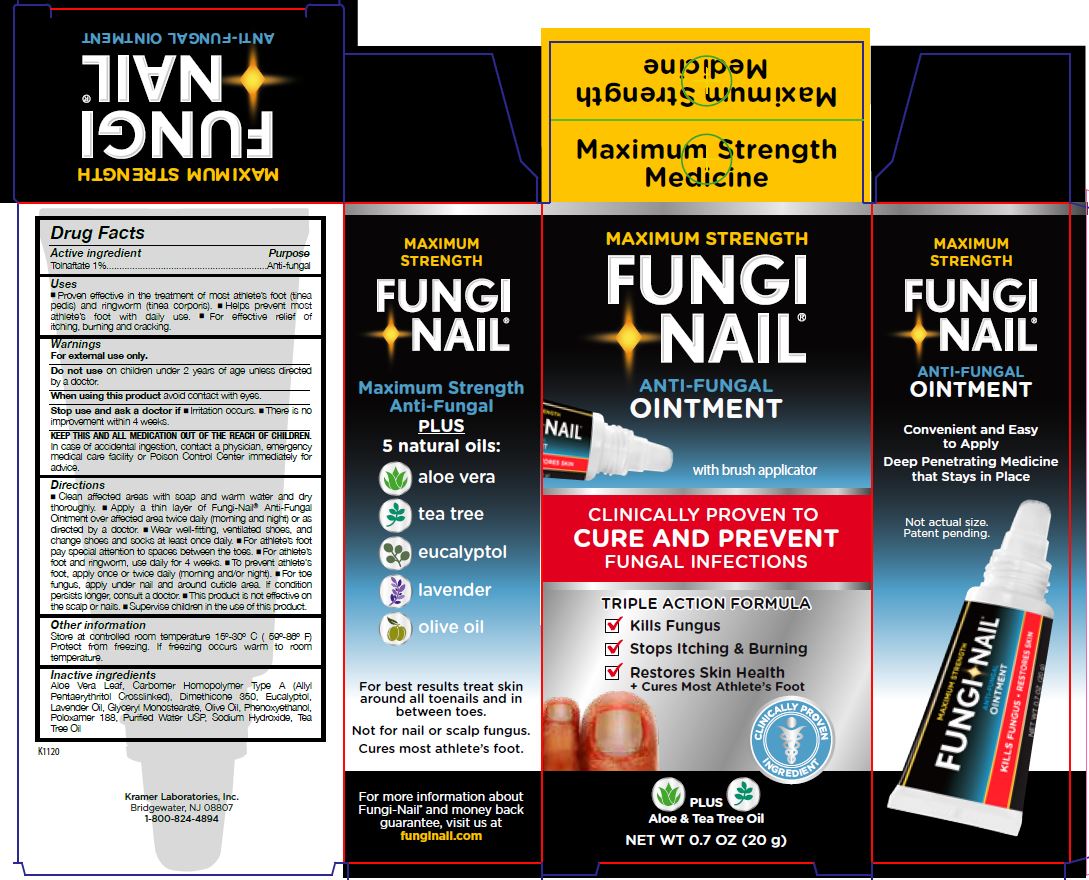 DRUG LABEL: Fungi Nail Toe and Foot
NDC: 55505-185 | Form: OINTMENT
Manufacturer: Kramer Laboratories
Category: otc | Type: HUMAN OTC DRUG LABEL
Date: 20250320

ACTIVE INGREDIENTS: Tolnaftate 1 g/100 g
INACTIVE INGREDIENTS: Aloe Vera Leaf; Carbomer Homopolymer Type A (Allyl Pentaerythritol Crosslinked); Dimethicone 350; Eucalyptol; Lavender Oil; Glyceryl Monostearate; Olive Oil; Phenoxyethanol; Poloxamer 188; Water; Sodium Hydroxide; Tea Tree Oil

Drug Facts

ACTIVE INGREDIENT

Active Ingredient | Purpose
Tolnaftate 1% | Anti-fungal

Uses
■ Proven effective in the treatment of most athlete’s foot (tinea pedis) and ringworm (tinea corporis). ■ Helps prevent most athlete's foot with daily use. ■ For effective relief of itching, burning and cracking.

Warnings

For external use only.

Do not use on children under 2 years of age unless directed by a doctor.

When using this product avoid contact with eyes.

Stop use and ask a doctor if ■ Irritation occurs. ■ There is no improvement within 4 weeks.

KEEP OUT OF REACH OF CHILDREN

KEEP THIS AND ALL MEDICATION OUT OF THE REACH OF CHILDREN.
In case of accidental ingestion, contact a physician, emergency medical care facility or Poison Control Center immediately for advice.

DOSAGE AND ADMINISTRATION

■ Clean affected areas with soap and warm water and dry thoroughly. ■ Apply a thin layer of Fungi-Nail® Anti-Fungal Ointment over affected area twice daily (morning and night) or as directed by a doctor. ■ Wear well-fitting, ventilated shoes, and change shoes and socks at least once daily. ■ For athlete’s foot pay special attention to spaces between the toes. ■ For athlete’s foot and ringworm, use daily for 4 weeks. ■ To prevent athlete's foot, apply once or twice daily (morning and/or night). ■ For toe fungus, apply under nail and around cuticle area. If condition persists longer, consult a doctor. ■ This product is not effective on the scalp or nails. ■ Supervise children in the use of this product.

Other information
Store at controlled room temperature 15º-30º C (59º-86º F) Protect from freezing. If freezing occurs warm to room temperature.

Inactive ingredients
Aloe Vera Leaf, Carbomer Homopolymer Type A (Allyl Pentaerythritol Crosslinked), Dimethicone 350, Eucalyptol, Lavender Oil, Glyceryl Monostearate, Olive Oil, Phenoxyethanol, Poloxamer 188, Purified Water USP, Sodium Hydroxide, Tea Tree Oil

PRINCIPAL DISPLAY PANEL

MAXIMUM STRENGTH
FUNGI-NAIL®
ANTI-FUNGAL
OINTMENT
with brush applicator
CLINICALLY PROVEN TO
CURE AND PREVENT
FUNGAL INFECTIONS
TRIPLE ACTION FORMULA
✓ Kills Fungus
✓ Stops Itching & Burning
✓ Restores Skin Health
+ Cures Most Athlete's Foot
CLINICALLY PROVEN INGREDIENT
PLUS
Aloe & Tea Tree Oil
NET WT 0.7 OZ (20 g)
Convenient and Easy to Apply
Deep Penetrating Medicine that Stays in Place
Not actual size.
Patent pending.
Maximum Strength
Anti-Fungal
PLUS
5 natural oils:
○ aloe vera
○ tea tree
○ eucalyptol
○ lavender
○ olive oil
For best results treat around all toenails and in between toes.
Not for Nail or scalp fungus.
Cures most athlete's foot.
For more information about Fungi-Nail® and money back guarantee, visit us at funginail.com
Kramer Laboratories, Inc.
Bridgewater, NJ 08807
1-800-824-4894
K1120